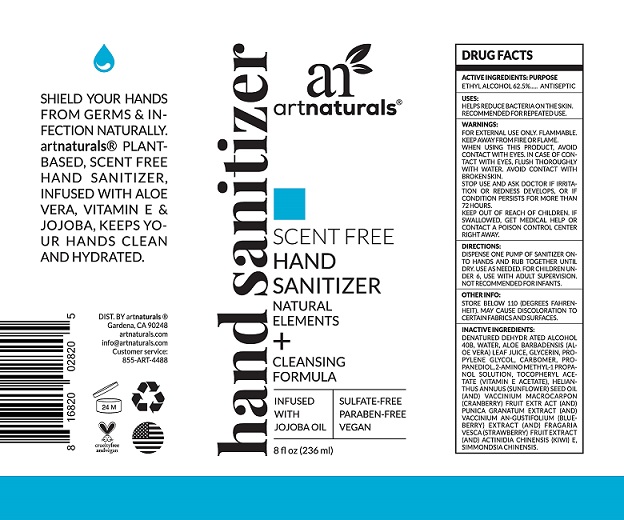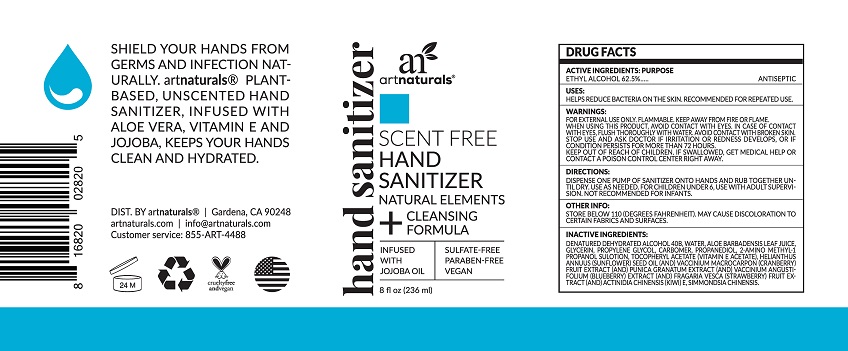 DRUG LABEL: Hand Sanitizer
NDC: 21839-845 | Form: GEL
Manufacturer: GORDON LABORATORIES,INC
Category: otc | Type: HUMAN OTC DRUG LABEL
Date: 20200501

ACTIVE INGREDIENTS: ALCOHOL 62.5 mL/100 mL
INACTIVE INGREDIENTS: PROPANEDIOL; BLUEBERRY; POMEGRANATE; CRANBERRY; ALPHA-TOCOPHEROL ACETATE; KIWI FRUIT; JOJOBA OIL; TEA TREE OIL; CARBOMER HOMOPOLYMER, UNSPECIFIED TYPE; SUNFLOWER OIL; WATER; GLYCERIN; ALOE VERA LEAF; PROPYLENE GLYCOL; FRAGARIA VESCA FRUIT; AMINOMETHYLPROPANOL

ARTNATURALS SCENT FREE HAND SANITIZER

Purpose

Antiseptic, Hand Sanitizer

USES:

HELPS REDUCE BACTERIA ON THE SKIN.

RECOMMENDED FOR REPEATED USE.

WARNINGS:

FOR EXTERNAL USE ONLY. FLAMMABLE

KEEP AWAY FROM FIRE OR FLAME.

WHEN USING THIS PRODUCT, AVOID

CONTACT WITH EYES. IN CASE OF CON-

TACT WITH EYES, FLUSH THOROUGHLY

WITH WATER. AVOID CONTACT WITH

BROKEN SKIN.

STOP USE AND ASK DOCTOR IF IRRITA-

TION OR REDNESS DEVELOPS, OR IF

CONDITION PERSISTS FOR MORE THAN

72 HOURS.

KEEP OUT OF REACH OF CHILDREN, IF

SWALLOWED, GET MEDICAL HELP OR

CONTACT A POISON CONTROL CENTER

RIGHT AWAY..

DIRECTIONS:

DISPENSE ONE PUMP OF SANITIZER ON-

TO HANDS AND RUB TOGETHER UNTIL

DRY. USE AS NEEDED. FOR CHILDREN UN-

DER 6, USE WITH ADULT SUPERVISION.

NOT RECOMMENDED FOR INFANTS.

OTHER INFO:

STORE BELOW 110 (DEGREES FAHREN-

HEIT). MAY CAUSE DISCOLORATON TO

CERTAIN FABRICS AND SURFACES

INACTIVE INGREDIENTS:

DENATURED DEHYDRATED ALCOHOL
40B, WATER, ALOE BARBADENSIS (AL-
OE VERA) LEAF JUICE, GLYCERIN, PRO-

PYLENE GLYCOL, CARBOMER, PRO-

PANEDIOL, 2-AMINO METHYL-1 PROPA-

NOL SOLUTION, TOCOPHERYL ACE-

TATE (VITAMIN E ACETATE), HELIAN-

THUS ANNUUS (SUNFLOWER) SEED OIL
(AND) VACCINIUM MACROCARPON
(CRANBERRY) FRUIT EXTRACT (AND)
PUNICA GRANATUM EXTRACT (AND)
VACCINIUM AN-GUSTIFOLIUM (BLUE-

BERRY) EXTRACT (AND) FRAGARIA
VESCA (STRAWBERRY) FRUIT EXTRACT
(AND) ACTINIDIA CHINENSIS (KIWI) E,
SIMMONDSIA CHINENSIS.

Package Label - Principal Display Panel

236 mL NDC 21839-845-01